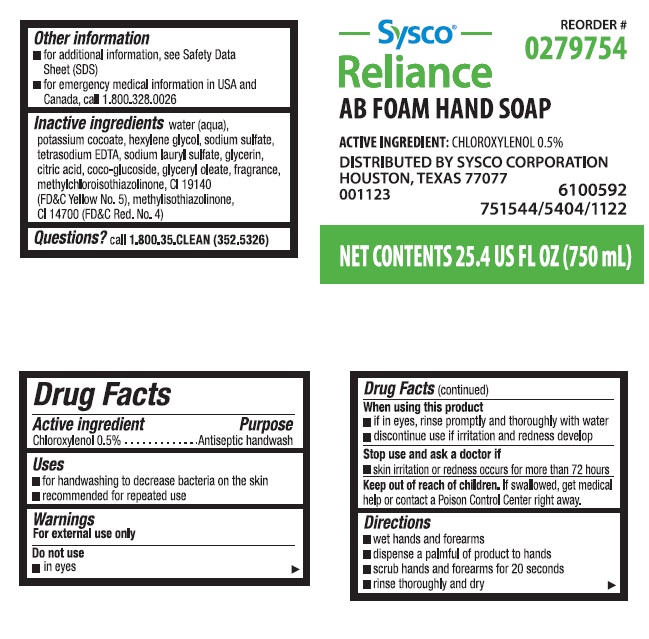 DRUG LABEL: Sysco
NDC: 47593-477 | Form: SOLUTION
Manufacturer: Ecolab Inc.
Category: otc | Type: HUMAN OTC DRUG LABEL
Date: 20251217

ACTIVE INGREDIENTS: CHLOROXYLENOL 0.5 mg/100 mL
INACTIVE INGREDIENTS: WATER; POTASSIUM COCOATE; HEXYLENE GLYCOL; SODIUM SULFATE; EDETATE SODIUM; SODIUM LAURYL SULFATE; GLYCERIN; CITRIC ACID MONOHYDRATE; COCO GLUCOSIDE; GLYCERYL OLEATE; METHYLCHLOROISOTHIAZOLINONE; FD&C YELLOW NO. 5; METHYLISOTHIAZOLINONE; FD&C RED NO. 4

Drug Facts

Active ingredient

Chloroxylenol, 0.5%

Purpose

Antiseptic handwash

Uses

- for handwashing to decrease bacteria on the skin
- recommended for repeated use

Warnings

For external use only

Do not use

- in eyes

When using this product

- if in eyes, rinse promptly and thoroughly with water
- discontinue use if irritation and redness develop

Stop use and ask a doctor if

- skin irritation or redness occurs for more than 72 hours

Keep out of reach of children. If swallowed, get medical help or contact a Poison Control Center right away.

Directions

- wet hands and forearms
- dispense a palmful of product to hands
- scrub hands and forearms for 20 seconds
- rinse thoroughly and dry

Other information

- for additional information, see Safety Data Sheet (SDS)
- for emergency medical information in USA and Canada, call 1.800.328.0026

INACTIVE INGREDIENT

Inactive ingredients water (aqua), potassium cocoate, hexylene glycol, sodium sulfate, tetrasodium EDTA, sodium lauryl sulfate, glycerin, citric acid, coco-glucoside, glyceryl oleate, fragrance, methylchloroisothiazolinone, CI 19140 (FDC Yellow No. 5), methylisothiazolinone, CI 14700 (FDC Red No. 4)

Questions? call 1.800.35.CLEAN (352.5326)

Principal display panel and representative label

Sysco Reorder #

Reliance 0279754

AB FOAM HAND SOAP

ACTIVE INGREDIENT: CHLOROXYLENOL 0.5%

DISTRIBUTED BY SYSCO CORPORATION

HOUSTON, TEXAS 77077

001123 6100592

751544/5404/1122

NET CONTENTS: 25.4 US FL OZ (750 mL)